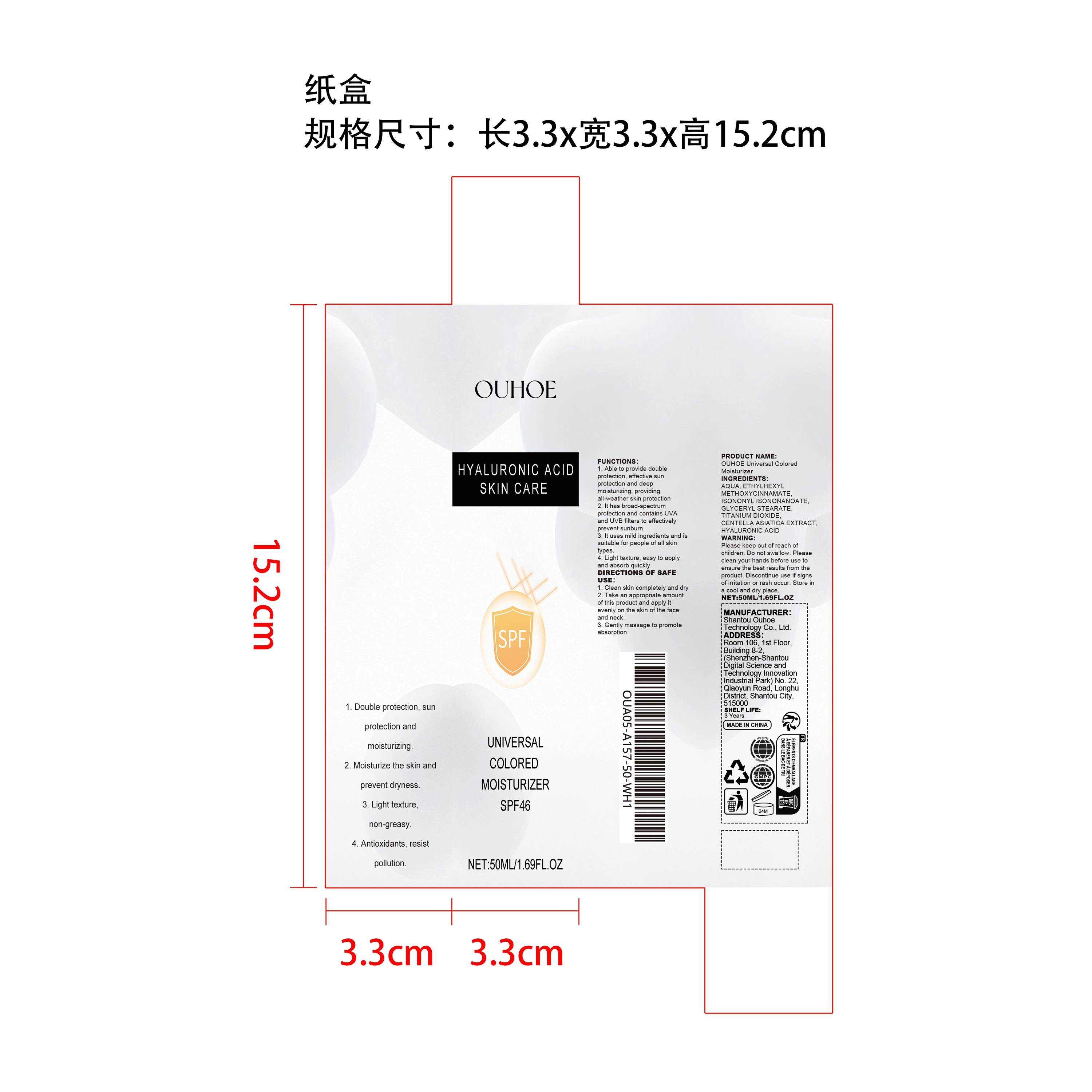 DRUG LABEL: OUHOE Universal Colored Moisturizer
NDC: 85163-016 | Form: CREAM
Manufacturer: Shantou Ouhoe Technology Co., Ltd.
Category: otc | Type: HUMAN OTC DRUG LABEL
Date: 20251218

ACTIVE INGREDIENTS: CENTELLA ASIATICA 0.01 mg/50 mg
INACTIVE INGREDIENTS: ISONONYL ISONONANOATE 2 mg/50 mg; AQUA 44.215 mg/50 mg; ETHYLHEXYL METHOXYCINNAMATE 2.5 mg/50 mg; TITANIUM DIOXIDE 0.5 mg/50 mg; HYALURONIC ACID 0.025 mg/50 mg; GLYCERYL STEARATE 0.75 mg/50 mg

ACTIVE INGREDIENT

CENTELLA ASIATICA EXTRACT

PURPOSE

1. Able to provide double protection, effective sun protection and deep moisturizing, providing all-weather skin protection

2. It has broad-spectrum protection and contains UVA and UVB filters to effectively prevent sunburn.

3. It uses mild ingredients and is suitable for people of all skin types.

4. Light texture, easy to apply and absorb quickly.

WHEN USING

1. Clean skin completely and dry

2. Take an appropriate amount of this product and apply it evenly on the skin of the face and neck.

3. Gently massage to promote absorption

WARNINGS

Please keep out of reach of children. Do not swallow.Please clean your hands before use to ensure the best results from the product. Discontinue use if signs of irritation or rash occur. Store in a cool and dry place.

DO NOT USE

Discontinue use if signs of irritation or rash occur.

STOP USE

Discontinue use if signs of irritation or rash occur.

Please keep out of reach of children.

STORAGE AND HANDLING

Store in a cool and dry place.

INACTIVE INGREDIENT

AQUA、ETHYLHEXYL METHOXYCINNAMATE、ISONONYL ISONONANOATE、GLYCERYL STEARATE、TITANIUM DIOXIDE、HYALURONIC ACID

DOSAGE AND ADMINISTRATION

1. Clean skin completely and dry

2. Take an appropriate amount of this product and apply it evenly on the skin of the face and neck.

3. Gently massage to promote absorption

INDICATIONS AND USAGE

1. Clean skin completely and dry

2. Take an appropriate amount of this product and apply it evenly on the skin of the face and neck.

3. Gently massage to promote absorption